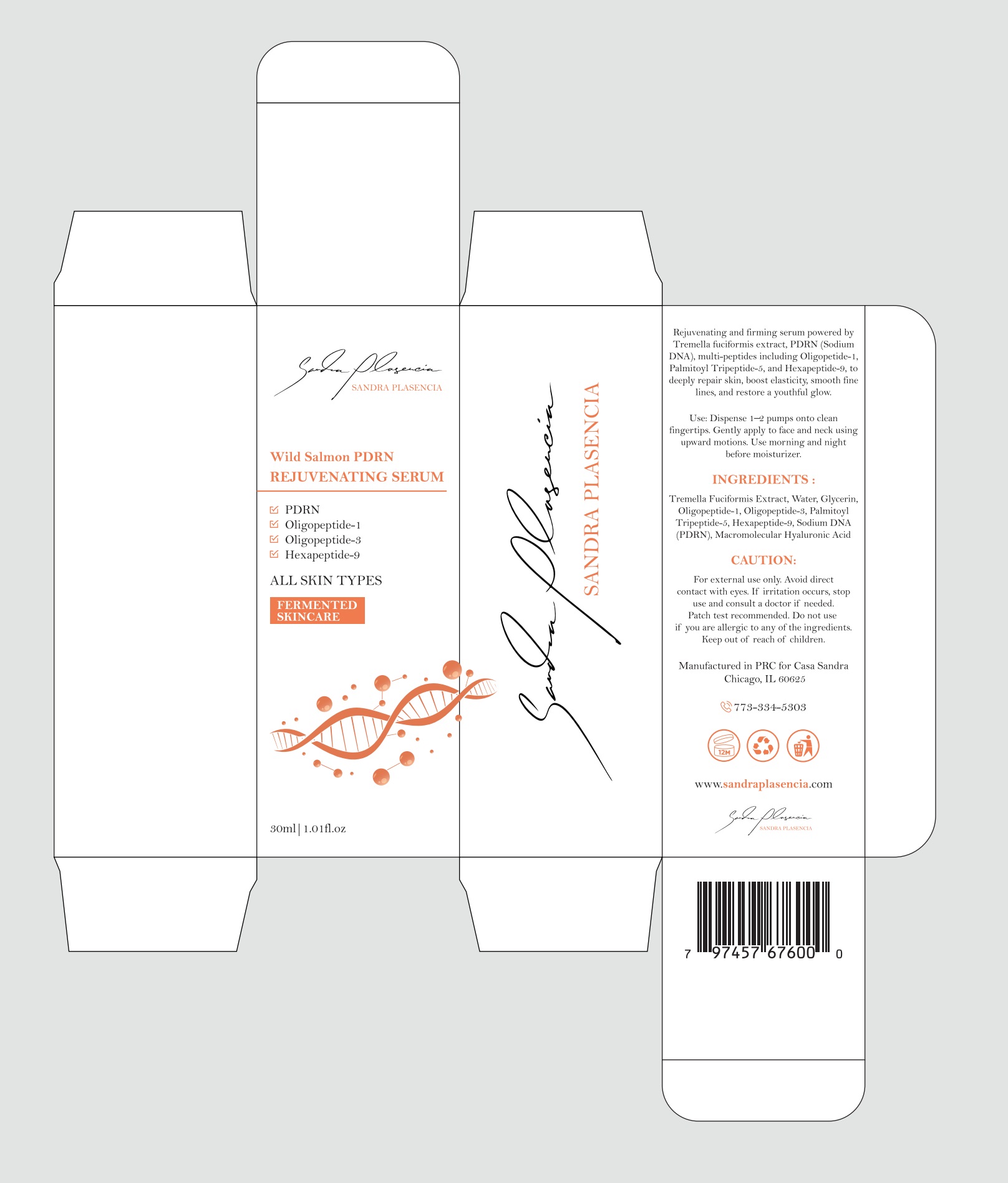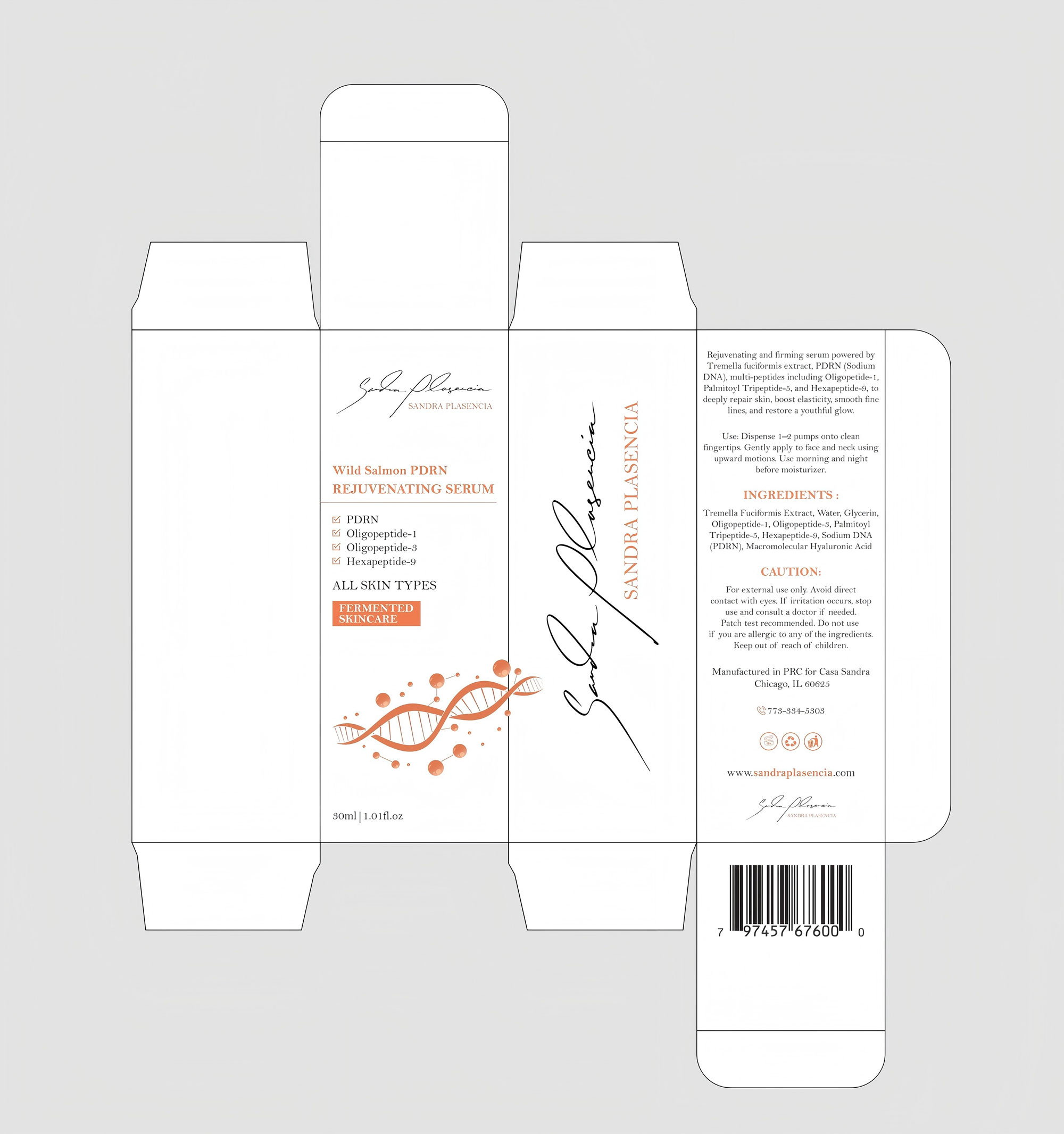 DRUG LABEL: Sandra Plasencia PDRN Rejuvenating Serum
NDC: 87036-035 | Form: LIQUID
Manufacturer: Guangzhou Meijiao Medical Biotechnology Co., Ltd.
Category: otc | Type: HUMAN OTC DRUG LABEL
Date: 20251127

ACTIVE INGREDIENTS: RH-OLIGOPEPTIDE-1 1 g/100 mL
INACTIVE INGREDIENTS: TREMELLA FUCIFORMIS WHOLE; WATER; GLYCERIN; RH-OLIGOPEPTIDE-33; PALMITOYL TRIPEPTIDE-5; HEXAPEPTIDE-9; HYALURONIC ACID

ACTIVE INGREDIENT

INACTIVE INGREDIENT

INGREDIENIS :
Tremella Fuciformis Extract, Water, Glycerin,Oligopeptide-1, Oligopeptide-3, PalmitoylTripeptide-5, Hexapeptide-9, Sodium DNA(PDRN),Macromolecular Hyaluronic Acid

PURPOSE

Rejuvenating and firming serum powered byTremella fuciformis extract, PDRN (SodiumDNA), multi-peptides including Oligopetide-1,Palmitoyl Tripeptide-5, and Hexapeptide-9, todeeply repair skin, boost elasticity, smooth finelines, and restore a youthful glow.

WARNINGS

CAUTION:
For external use only. Avoid directcontact with eyes. If irritation occurs, stopuse and consult a doctor if needed.Patch test recommended. Do not useif you are allergic to any of the ingredients.Keep out of reach of children.

DO NOT USE

CAUTION:
For external use only. Avoid directcontact with eyes. If irritation occurs, stopuse and consult a doctor if needed.Patch test recommended. Do not useif you are allergic to any of the ingredients.Keep out of reach of children.

KEEP OUT OF REACH OF CHILDREN

CAUTION:
For external use only. Avoid directcontact with eyes. If irritation occurs, stopuse and consult a doctor if needed.Patch test recommended. Do not useif you are allergic to any of the ingredients.Keep out of reach of children.

STOP USE

CAUTION:
For external use only. Avoid directcontact with eyes. If irritation occurs, stopuse and consult a doctor if needed.Patch test recommended. Do not useif you are allergic to any of the ingredients.Keep out of reach of children.

INDICATIONS AND USAGE

Use: Dispense 1-2 pumps onto cleanfingertips. Gently apply to face and neck usingupward motions.Use morning and nightbefore moisturizer,

WHEN USING

Use: Dispense 1-2 pumps onto cleanfingertips. Gently apply to face and neck usingupward motions.Use morning and nightbefore moisturizer,

DOSAGE AND ADMINISTRATION

Use: Dispense 1-2 pumps onto cleanfingertips. Gently apply to face and neck usingupward motions.Use morning and nightbefore moisturizer,

PACKAGE LABEL

SANDRA PLASENCIA
Wild Salmon PDRN
REJUVENATING SERUM
M PDRN
6 0ligopeptide-1
Oligopeptide-3
Ã Hexapeptide-9
ALL SKIN TYPES
FERMENTEDSKINCARE
VIONISVId VGNVS
Rejuvenating and firming serum powered byTremella fuciformis extract,PDRN(SodiumDNA),multi-peptides including Oligopetide-1Palmitoyl Tripeptide-5, and Hexapeptide-9, todeeply repair skin, boost elasticity, smooth finelines, and restore a youthful glow,
Use: Dispense 1-2 pumps onto cleanfingertips, Gently apply to face and neck usingupward motions.Use morning and nightbefore moisturizer,
INGREDIENTS
Tremella Fuciformis Extract, Water, GlycerinOligopeptide-1,Oligopeptide-$, PalmitoylTripeptide-5, Hexapeptide-9, Sodium DNA(PDRN),Macromolecular Hyaluronic Acid
CAUTION:
For external use only, Avoid directcontact with eyes, If irritation occurs, stopuse and consult a doctor if needed.Patch test recommended.Do not useif you are allergic to any of the ingredients.Keep out of reach of children.
Manufactured in PRC for Casa SandraChicago,Il 60625
G773-334-5303
www.sandraplasencia.com